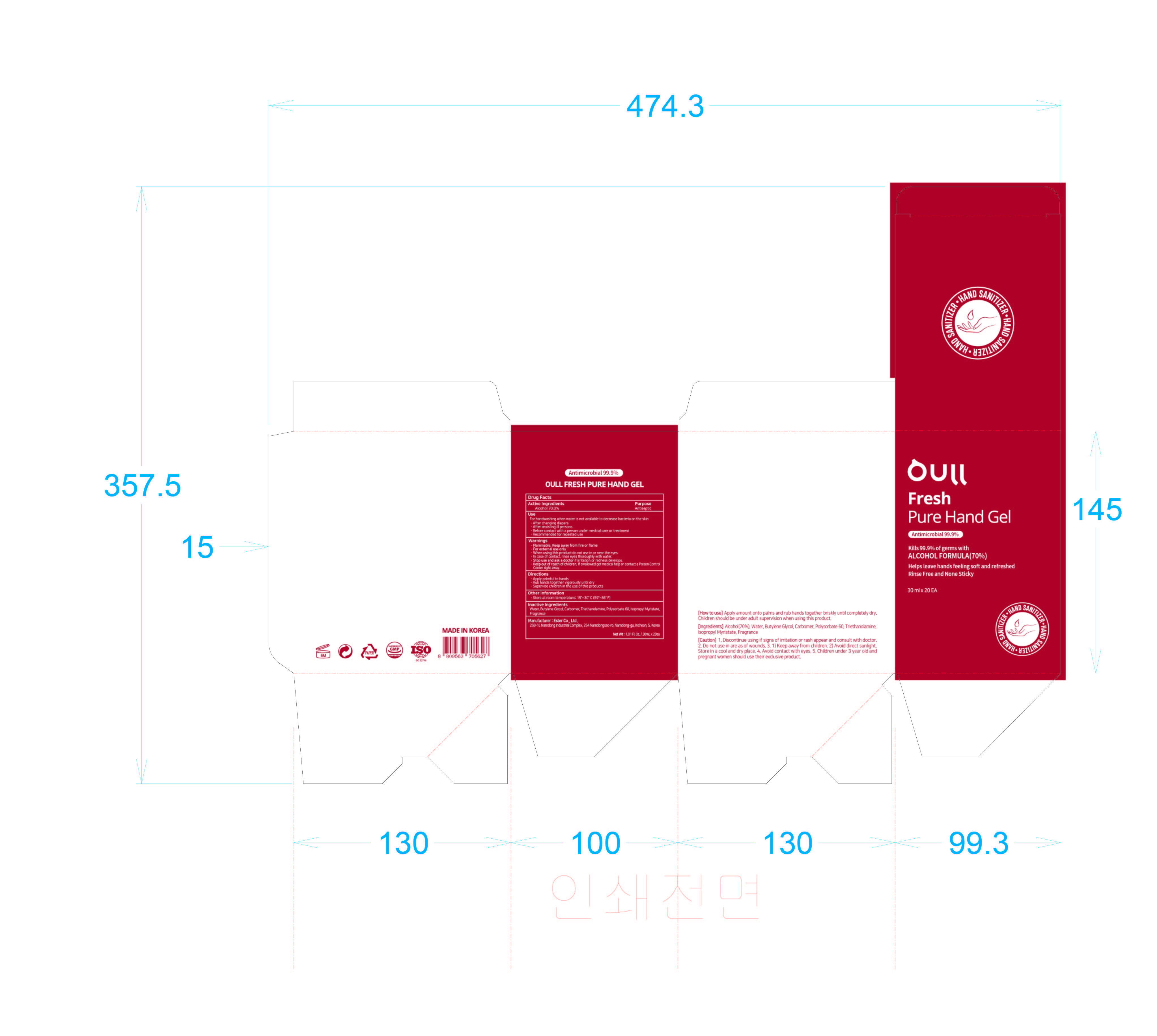 DRUG LABEL: OULL FRESH PURE HAND Gel
NDC: 74004-137 | Form: GEL
Manufacturer: Ester Co., Ltd.
Category: otc | Type: HUMAN OTC DRUG LABEL
Date: 20201111

ACTIVE INGREDIENTS: ALCOHOL 21 g/30 mL
INACTIVE INGREDIENTS: POLYSORBATE 60; BUTYLENE GLYCOL; ISOPROPYL MYRISTATE; CARBOMER HOMOPOLYMER, UNSPECIFIED TYPE; WATER; TROLAMINE

[Ester Co., Ltd.-OULL FRESH PURE HAND GEL] 30 ml X 20 : 74004-137-20